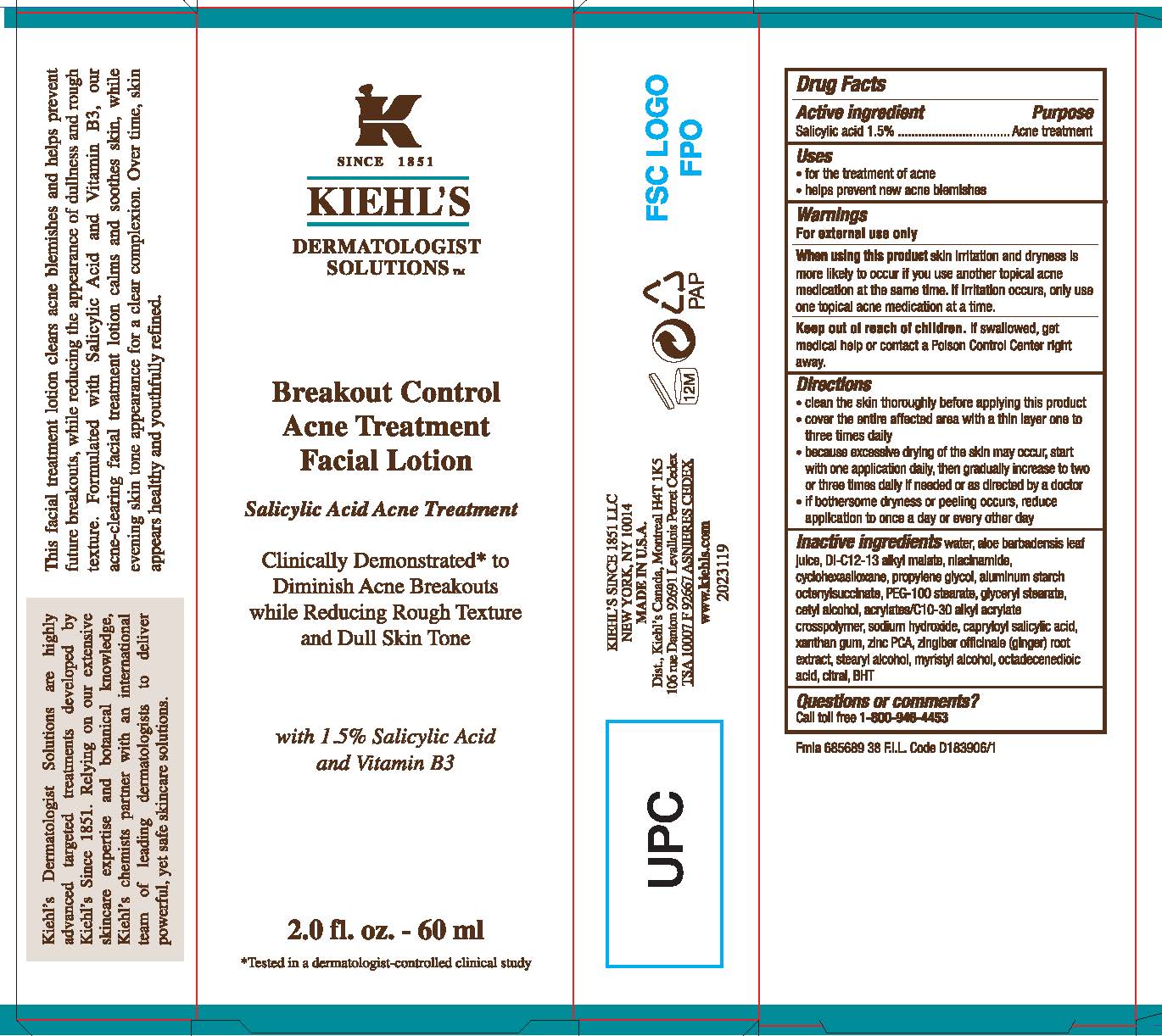 DRUG LABEL: Kiehls Since 1851 Dermatologist Solutions Breakout Control Acne Treatment Facial
NDC: 49967-875 | Form: LOTION
Manufacturer: L'Oreal USA Products Inc
Category: otc | Type: HUMAN OTC DRUG LABEL
Date: 20231230

ACTIVE INGREDIENTS: SALICYLIC ACID 15 mg/1 mL
INACTIVE INGREDIENTS: WATER; NIACINAMIDE; PROPYLENE GLYCOL; ALUMINUM STARCH OCTENYLSUCCINATE; PEG-100 STEARATE; CETYL ALCOHOL; SODIUM HYDROXIDE; CAPRYLOYL SALICYLIC ACID; XANTHAN GUM; STEARYL ALCOHOL; MYRISTYL ALCOHOL; OCTADECENEDIOIC ACID; CITRAL

Drug Facts

Active ingredient

Salicylic acid 1.5%

Purpose

Acne treatment

Uses

- for the treatment of acne
- helps prevent new acne blemishes

Warnings

For external use only

When using this product

skin irritation and dryness is more likely to occur if you use another topical acne medication at the same time. If irritation occurs, only use one topical acne medication at a time.

Keep out of reach of children.

If swallowed, get medical help or contact a Poison Control Center right away.

Directions

- clean the skin thoroughly before applying this product
- cover the entire affected area with a thin layer one to three times daily
- because excessive drying of the skin may occur, start with one application daily, then gradually increase to two or three times daily if needed or as directed by a doctor
- if bothersome dryness or peeling occurs, reduce application to once a day or every other day

Inactive ingredients

water, aloe barbadensis leaf juice, di-C12-13 alkyl malate, niacinamide, cyclohexasiloxane, propylene glycol, aluminum starch octenylsuccinate, PEG-100 stearate, glyceryl stearate, cetyl alcohol, acrylates/C10-30 alkyl acrylate crosspolymer, sodium hydroxide, capryloyl salicylic acid, xanthan gum, zinc PCA, zingiber officinale (ginger) root extract, stearyl alcohol, myristyl alcohol, citric acid, potassium sorbate, octadecenedioic acid, sodium benzoate, citral, BHT

Questions or comments?

Call toll free 1-800-946-4453